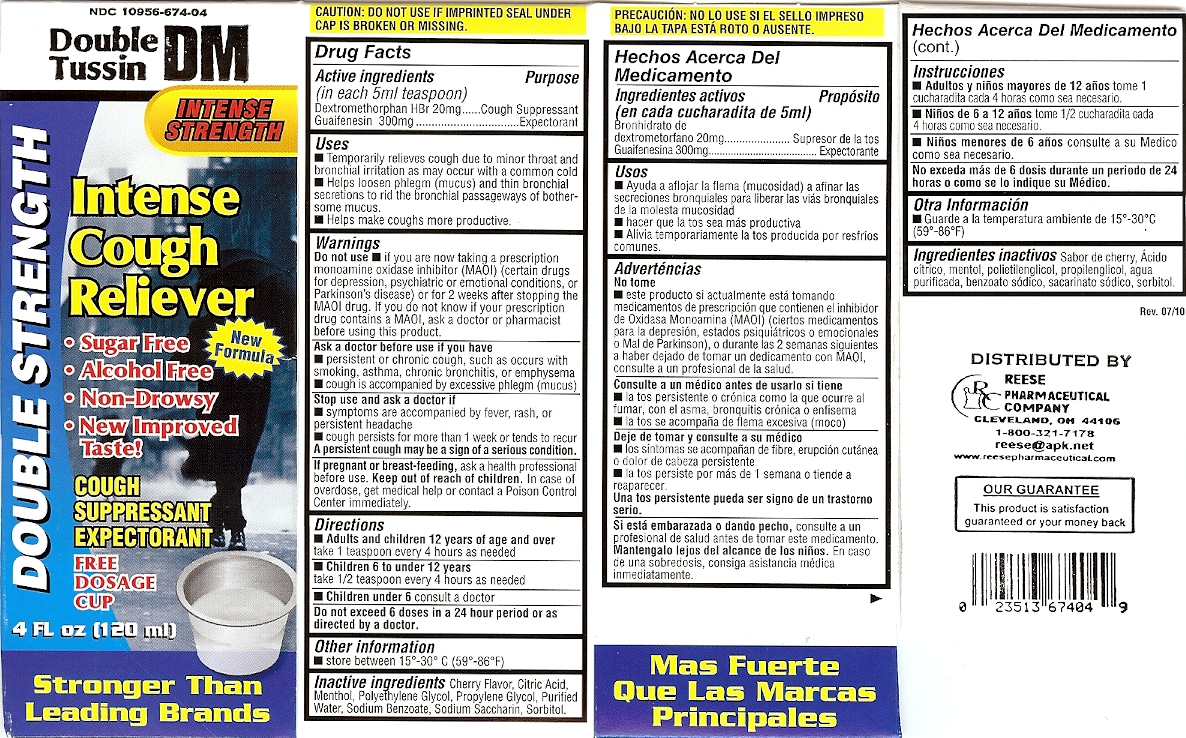 DRUG LABEL: Double Tussin Intense Cough Reliever
NDC: 10956-674 | Form: LIQUID
Manufacturer: Reese Pharmaceutical Co
Category: otc | Type: HUMAN OTC DRUG LABEL
Date: 20110126

ACTIVE INGREDIENTS: DEXTROMETHORPHAN HYDROBROMIDE 20 mg/5 mL; Guaifenesin 300 mg/5 mL
INACTIVE INGREDIENTS: POLYETHYLENE GLYCOL ; SODIUM BENZOATE; SORBITOL

DRUG FACTS

Active ingredient per 5ml teaspoon
Dextromethorphan Hydrobromide 20mg Cough Suppressant
Guaifenesin 300mg Expectorant

INDICATIONS AND USAGE

Uses. temporarily relieves cough due to minor throat and bronchial irritation
as may occur with a common cold • helps loosen phlegm (mucus) and thin
bronchial secretions to rid the bronchial passageways of bothersome mucus
• helps make coughs more productive

Do not use if you are now taking a prescription monoamine oxidase (inhiMor~MAIO)
Certain drugs for depression, psychiatric or emotional conditioners or Parkinson's disease
or for 2 weeks after stopping MAIO drug, If you do not know if your prescription drug contains
an MAIO, ask your doctor or pharmacist before using this product

Ask doctor before use if you have
persistent or chronic cough, such as occurs with smoking, asthma, bronchitis or emphysma
cough is accompanied by excessive phlegm (mucous)

Stop use and ask doctor if
Symptoms are accompanied by fever, rash or persistent headache
cough persists for more than 1 week or tends to recur
A persistent cough may be a sign of a serious condition

PREGNANCY OR BREAST FEEDING

If pregnant or breastfeeding, ask a health professional before use

Keep out of reach of children, In case of overdose, get medical help or contact a Poison Center immediately

Directions
• Adults and children 12 years of age and over:
take 1 tablet every 4 hours as needed
• Children 6 to 10 under 12 years of age: take 1/2 tablet every 4 hours as needed
• Children under 6 years of age: consult a doctor
Do not exceed 6 doses in a 24 hour period or as directed by a doctor
Other information store at 15'- 30' C (59'- 86'F)

Purpose
Dextromethorphan Hydrobromide Cough Suppressant
Guaifenesin Expectorant

INACTIVE INGREDIENT

Cherry Flavor,Citric Acid,Menthol,Polyethylene Glycol,Propylene Glycol,Purified Water,
Sodium Benzoate,Sodium Saccharin,Sorbitol.